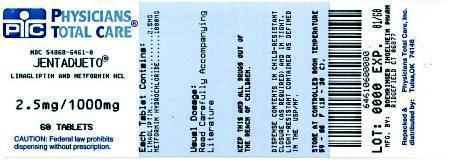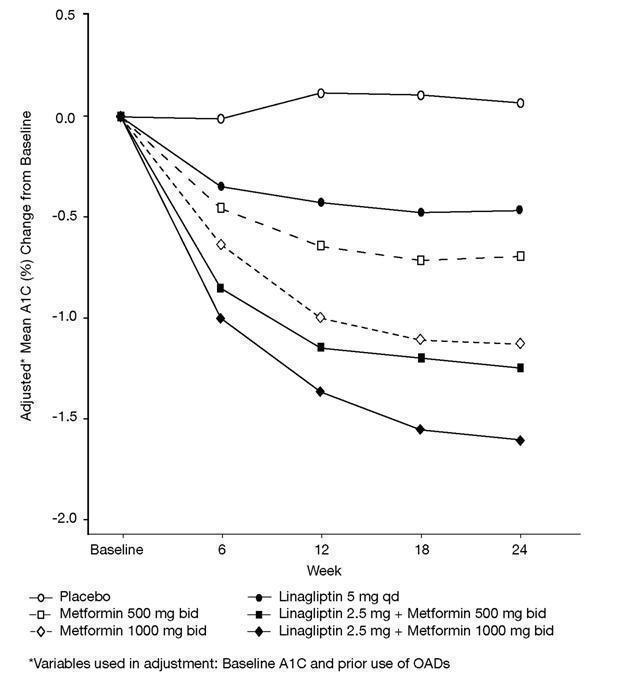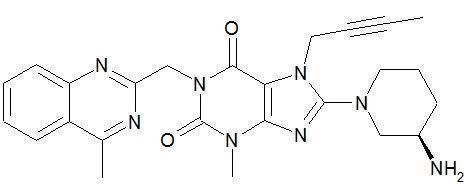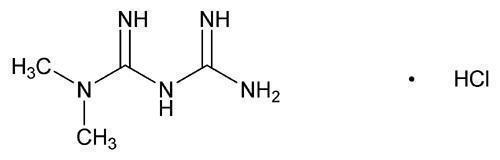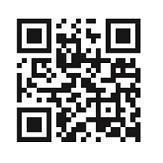 DRUG LABEL: Jentadueto
NDC: 54868-6461 | Form: TABLET, FILM COATED
Manufacturer: Physicians Total Care, Inc.
Category: prescription | Type: HUMAN PRESCRIPTION DRUG LABEL
Date: 20150506

ACTIVE INGREDIENTS: linagliptin 2.5 mg/1 1; metformin hydrochloride 1000 mg/1 1
INACTIVE INGREDIENTS: arginine; starch, corn; copovidone; SILICON DIOXIDE; magnesium stearate; titanium dioxide; propylene glycol; hypromelloses; talc; FERRIC OXIDE RED

HIGHLIGHTS OF PRESCRIBING INFORMATION

These highlights do not include all the information needed to use JENTADUETO safely and effectively. See full prescribing information for JENTADUETO.
Jentadueto® (linagliptin and metformin hydrochloride) tablets
Initial U.S. Approval: 2012

WARNING: RISK OF LACTIC ACIDOSIS

See full prescribing information for complete boxed warning.

- Lactic acidosis can occur due to metformin accumulation. The risk increases with conditions such as renal impairment, sepsis, dehydration, excess alcohol intake, hepatic impairment, and acute congestive heart failure. (5.1)
- Symptoms include malaise, myalgias, respiratory distress, increasing somnolence, and nonspecific abdominal distress. Laboratory abnormalities include low pH, increased anion gap, and elevated blood lactate. (5.1)
- If acidosis is suspected, discontinue JENTADUETO and hospitalize the patient immediately (5.1)

RECENT MAJOR CHANGES

Dosage and Administration
 | Concomitant Use with an Insulin Secretagogue (e.g., Sulfonylurea) or with Insulin (2.2) | 9/2013
Contraindications (4) | 5/2014
Warnings and Precautions
 | Use with Medications Known to Cause Hypoglycemia (5.5) | 9/2013
 | Hypersensitivity Reactions (5.6) | 5/2014

1 INDICATIONS AND USAGE

JENTADUETO is a dipeptidyl peptidase-4 (DPP-4) inhibitor and biguanide combination product indicated as an adjunct to diet and exercise to improve glycemic control in adults with type 2 diabetes mellitus when treatment with both linagliptin and metformin is appropriate (1.1)

Important limitations of use:

- Not for treatment of type 1 diabetes or diabetic ketoacidosis (1.2)
- Has not been studied in patients with a history of pancreatitis (1.2)

2 DOSAGE AND ADMINISTRATION

- Individualize the starting dose of JENTADUETO based on the patient's current regimen (2.1)
- The maximum recommended dose is 2.5 mg linagliptin/1000 mg metformin twice daily (2.1)
- Should be given twice daily with meals, with gradual dose escalation to reduce the gastrointestinal side effects due to metformin (2.1)

3 DOSAGE FORMS AND STRENGTHS

Tablets:
2.5 mg linagliptin/500 mg metformin hydrochloride
2.5 mg linagliptin/850 mg metformin hydrochloride
2.5 mg linagliptin/1000 mg metformin hydrochloride (3)

4 CONTRAINDICATIONS

- Renal impairment (4)
- Metabolic acidosis, including diabetic ketoacidosis (4)
- History of hypersensitivity reaction to linagliptin, such as anaphylaxis, angioedema, exfoliative skin conditions, urticaria, or bronchial hyperreactivity (4)
- Hypersensitivity to metformin (4)

5 WARNINGS AND PRECAUTIONS

- Lactic acidosis: Warn against excessive alcohol use. JENTADUETO is not recommended in hepatic impairment or hypoxic states and is contraindicated in renal impairment. Ensure normal renal function before initiating and at least annually thereafter. (5.1, 5.3, 5.4, 5.8, 5.9)
- There have been postmarketing reports of acute pancreatitis, including fatal pancreatitis. If pancreatitis is suspected, promptly discontinue JENTADUETO. (5.2)
- Temporarily discontinue JENTADUETO in patients undergoing radiologic studies with intravascular administration of iodinated contrast materials or any surgical procedures necessitating restricted intake of food and fluids (5.3)
- Hypoglycemia: When used with an insulin secretagogue (e.g., sulfonylurea (SU) or insulin, consider lowering the dose of the insulin secretagogue or insulin to reduce the risk of hypoglycemia (2.2, 5.5)
- There have been postmarketing reports of serious hypersensitivity reactions in patients treated with linagliptin (one of the components of JENTADUETO) including anaphylaxis, angioedema, and exfoliative skin conditions. In such cases, promptly discontinue JENTADUETO, assess for other potential causes, institute appropriate monitoring and treatment, and initiate alternative treatment for diabetes. (5.6)
- Vitamin B12 deficiency: Metformin may lower vitamin B12 levels. Monitor hematologic parameters annually (5.7)
- Macrovascular outcomes: No conclusive evidence of macrovascular risk reduction with JENTADUETO or any other antidiabetic drug (5.10)

6 ADVERSE REACTIONS

- Adverse reactions reported in ≥5% of patients treated with JENTADUETO and more commonly than in patients treated with placebo are nasopharyngitis and diarrhea (6.1)
- Hypoglycemia was more commonly reported in patients treated with the combination of JENTADUETO and SU compared with those treated with the combination of SU and metformin (6.1)

To report SUSPECTED ADVERSE REACTIONS, contact Boehringer Ingelheim Pharmaceuticals, Inc. at 1-800-542-6257 or 1-800-459-9906 TTY, or FDA at 1-800-FDA-1088 or www.fda.gov/medwatch.

7 DRUG INTERACTIONS

- Cationic drugs eliminated by renal tubular secretion: May reduce metformin elimination. Use with caution. (7.1)
- Strong P-glycoprotein/CYP3A4 inducer: The efficacy of JENTADUETO may be reduced when administered in combination (e.g., rifampin). Use of alternative treatments is strongly recommended. (7.2)

8 USE IN SPECIFIC POPULATIONS

- Pregnancy: JENTADUETO tablets should be used during pregnancy only if clearly needed. (8.1)
- Nursing mothers: Caution should be exercised when JENTADUETO is administered to a nursing woman (8.3)

FULL PRESCRIBING INFORMATION

WARNING: RISK OF LACTIC ACIDOSIS

Lactic acidosis is a rare, but serious, complication that can occur due to metformin accumulation. The risk increases with conditions such as renal impairment, sepsis, dehydration, excess alcohol intake, hepatic impairment, and acute congestive heart failure.

The onset is often subtle, accompanied only by nonspecific symptoms such as malaise, myalgias, respiratory distress, increasing somnolence, and nonspecific abdominal distress.

Laboratory abnormalities include low pH, increased anion gap, and elevated blood lactate.

If acidosis is suspected, JENTADUETO should be discontinued and the patient hospitalized immediately [see Warnings and Precautions (5.1)].

1 INDICATIONS AND USAGE

1.1 Indication

JENTADUETO tablets are indicated as an adjunct to diet and exercise to improve glycemic control in adults with type 2 diabetes mellitus when treatment with both linagliptin and metformin is appropriate [see Dosage and Administration (2.1) and Clinical Studies (14.1)].

1.2 Important Limitations of Use

JENTADUETO should not be used in patients with type 1 diabetes or for the treatment of diabetic ketoacidosis, as it would not be effective in these settings.

JENTADUETO has not been studied in patients with a history of pancreatitis. It is unknown whether patients with a history of pancreatitis are at an increased risk for the development of pancreatitis while using JENTADUETO [see Warnings and Precautions (5.2)].

2 DOSAGE AND ADMINISTRATION

2.1 Recommended Dosing

The dosage of JENTADUETO should be individualized on the basis of both effectiveness and tolerability, while not exceeding the maximum recommended dose of 2.5 mg linagliptin/1000 mg metformin hydrochloride twice daily. JENTADUETO should be given twice daily with meals. Dose escalation should be gradual to reduce the gastrointestinal (GI) side effects associated with metformin use. For available dosage forms and strengths see [Dosage Forms and Strengths (3)].

Recommended starting dose:

- In patients currently not treated with metformin, initiate treatment with 2.5 mg linagliptin/500 mg metformin hydrochloride twice daily
- In patients already treated with metformin, start with 2.5 mg linagliptin and the current dose of metformin taken at each of the two daily meals (e.g., a patient on metformin 1000 mg twice daily would be started on 2.5 mg linagliptin/1000 mg metformin hydrochloride twice daily with meals).
- Patients already treated with linagliptin and metformin individual components may be switched to JENTADUETO containing the same doses of each component.

No studies have been performed specifically examining the safety and efficacy of JENTADUETO in patients previously treated with other oral antihyperglycemic agents and switched to JENTADUETO. Any change in therapy of type 2 diabetes mellitus should be undertaken with care and appropriate monitoring as changes in glycemic control can occur.

2.2 Concomitant Use with an Insulin Secretagogue (e.g., Sulfonylurea) or with Insulin

When JENTADUETO is used in combination with an insulin secretagogue (e.g., sulfonylurea) or with insulin, a lower dose of the insulin secretagogue or insulin may be required to reduce the risk of hypoglycemia [see Warnings and Precautions (5.5)].

3 DOSAGE FORMS AND STRENGTHS

JENTADUETO is a combination of linagliptin and metformin hydrochloride. JENTADUETO tablets are available in the following dosage forms and strengths:

- 2.5 mg linagliptin/1000 mg metformin hydrochloride tablets are light pink, oval, biconvex tablets debossed with “D2/1000” on one side and the Boehringer Ingelheim logo on the other side

4 CONTRAINDICATIONS

JENTADUETO is contraindicated in patients with:

- Renal impairment (e.g., serum creatinine ≥1.5 mg/dL for men, ≥1.4 mg/dL for women, or abnormal creatinine clearance), which may also result from conditions such as cardiovascular collapse (shock), acute myocardial infarction, and septicemia [see Warnings and Precautions (5.1, 5.3)]
- Acute or chronic metabolic acidosis, including diabetic ketoacidosis. Diabetic ketoacidosis should be treated with insulin [see Warnings and Precautions (5.1)]
- A history of hypersensitivity reaction to linagliptin, such as anaphylaxis, angioedema, exfoliative skin conditions, urticaria, or bronchial hyperreactivity [see Warnings and Precautions (5.6) and Adverse Reactions (6.1)]
- Hypersensitivity to metformin

5 WARNINGS AND PRECAUTIONS

5.1 Lactic Acidosis

Metformin

Lactic acidosis is a serious, metabolic complication that can occur due to metformin accumulation during treatment with JENTADUETO and is fatal in approximately 50% of cases. Lactic acidosis may also occur in association with a number of pathophysiologic conditions, including diabetes mellitus, and whenever there is significant tissue hypoperfusion and hypoxemia. Lactic acidosis is characterized by elevated blood lactate levels (>5 mmol/L), decreased blood pH, electrolyte disturbances with an increased anion gap, and an increased lactate/pyruvate ratio. When metformin is implicated as the cause of lactic acidosis, metformin plasma levels of >5 µg/mL are generally found.

The reported incidence of lactic acidosis in patients receiving metformin is approximately 0.03 cases/1000 patient-years, (with approximately 0.015 fatal cases/1000 patient-years). In more than 20,000 patient-years exposure to metformin in clinical trials, there were no reports of lactic acidosis. Reported cases have occurred primarily in diabetic patients with significant renal impairment, including both intrinsic renal disease and renal hypoperfusion, often in the setting of multiple concomitant medical/surgical problems and multiple concomitant medications. Patients with congestive heart failure requiring pharmacologic management, particularly when accompanied by hypoperfusion and hypoxemia due to unstable or acute failure, are at increased risk of lactic acidosis. The risk of lactic acidosis increases with the degree of renal impairment and the patient’s age. The risk of lactic acidosis may, therefore, be significantly decreased by regular monitoring of renal function in patients taking metformin. In particular, treatment of the elderly should be accompanied by careful monitoring of renal function. Metformin treatment should not be initiated in any patient unless measurement of creatinine clearance demonstrates that renal function is not reduced. In addition, metformin should be promptly withheld in the presence of any condition associated with hypoxemia, dehydration, or sepsis. Because impaired hepatic function may significantly limit the ability to clear lactate, metformin should be avoided in patients with clinical or laboratory evidence of hepatic impairment. Patients should be cautioned against excessive alcohol intake when taking metformin, since alcohol potentiates the effects of metformin on lactate metabolism. In addition, metformin should be temporarily discontinued prior to any intravascular radiocontrast study and for any surgical procedure necessitating restricted intake of food or fluids. Use of topiramate, a carbonic anhydrase inhibitor, in epilepsy and migraine prophylaxis may cause dose-dependent metabolic acidosis and may exacerbate the risk of metformin-induced lactic acidosis [see Drug Interactions (7.1) and Clinical Pharmacology (12.3)].

The onset of lactic acidosis is often subtle, and accompanied by nonspecific symptoms such as malaise, myalgias, respiratory distress, increasing somnolence, and nonspecific abdominal distress. More severe acidosis may be associated with signs such as hypothermia, hypotension, and resistant bradyarrhythmias. Patients should be educated to recognize and promptly report these symptoms. If present, JENTADUETO should be discontinued until lactic acidosis is ruled out. Gastrointestinal symptoms, which are commonly reported during initiation of metformin therapy are less frequently observed in subjects on a chronic, stable, dose of metformin. Gastrointestinal symptoms in subjects on chronic, stable, dose of metformin could be caused by lactic acidosis or other serious disease.

To rule out lactic acidosis, serum electrolytes, ketones, blood glucose, blood pH, lactate levels, and blood metformin levels may be useful. Levels of fasting venous plasma lactate above the upper limit of normal but less than 5 mmol/L in patients taking metformin do not necessarily indicate impending lactic acidosis and may be due to other mechanisms, such as poorly-controlled diabetes or obesity, vigorous physical activity, or technical problems in sample handling.

Lactic acidosis should be suspected in any diabetic patient with metabolic acidosis lacking evidence of ketoacidosis (ketonuria and ketonemia). Lactic acidosis is a medical emergency that must be treated in a hospital setting. In a patient with lactic acidosis who is taking metformin, the drug should be discontinued immediately and supportive measures promptly instituted. Metformin is dialyzable (clearance of up to 170 mL/min under good hemodynamic conditions) and prompt hemodialysis is recommended to remove the accumulated metformin and correct the metabolic acidosis. Such management often results in prompt reversal of symptoms and recovery [see Boxed Warning].

5.2 Pancreatitis

There have been postmarketing reports of acute pancreatitis, including fatal pancreatitis, in patients taking linagliptin. Take careful notice of potential signs and symptoms of pancreatitis. If pancreatitis is suspected, promptly discontinue JENTADUETO and initiate appropriate management. It is unknown whether patients with a history of pancreatitis are at increased risk for the development of pancreatitis while using JENTADUETO.

5.3 Monitoring of Renal Function

Although linagliptin undergoes minimal renal excretion, metformin is known to be substantially excreted by the kidney. The risk of metformin accumulation and lactic acidosis increases with the degree of renal impairment. Therefore, JENTADUETO is contraindicated in patients with renal impairment.

Before initiation of therapy with JENTADUETO and at least annually thereafter, renal function should be assessed and verified to be normal. In patients in whom development of renal impairment is anticipated (e.g., elderly), renal function should be assessed more frequently and JENTADUETO discontinued if evidence of renal impairment is present.

Linagliptin may be continued as a single entity tablet at the same total daily dose of 5 mg if JENTADUETO is discontinued due to evidence of renal impairment. No dose adjustment of linagliptin is recommended in patients with renal impairment.

Use of concomitant medications that may affect renal function or metformin disposition:

Concomitant medication(s) that may affect renal function or result in significant hemodynamic change or interfere with the disposition of metformin should be used with caution [see Drug Interactions (7.1) and Clinical Pharmacology (12.3)].

Radiological studies and surgical procedures:

Radiologic studies involving the use of intravascular iodinated contrast materials (e.g., intravenous urogram, intravenous cholangiography, angiography, and computed tomography) can lead to acute alteration of renal function and have been associated with lactic acidosis in patients receiving metformin. Therefore, in patients in whom any such study is planned, JENTADUETO should be temporarily discontinued at the time of or prior to the procedure, and withheld for 48 hours subsequent to the procedure and reinstituted only after renal function has been confirmed to be normal.

JENTADUETO should be temporarily discontinued for any surgical procedure (except minor procedures not associated with restricted intake of food and fluids) and should not be restarted until the patient’s oral intake has resumed and renal function has been evaluated as normal.

5.4 Impaired Hepatic Function

Because impaired hepatic function has been associated with some cases of lactic acidosis with metformin therapy, JENTADUETO should generally be avoided in patients with clinical or laboratory evidence of hepatic disease [see Warnings and Precautions (5.1)].

5.5 Use with Medications Known to Cause Hypoglycemia

Linagliptin

Insulin secretagogues and insulin are known to cause hypoglycemia. The use of linagliptin in combination with an insulin secretagogue (e.g., sulfonylurea) was associated with a higher rate of hypoglycemia compared with placebo in a clinical trial [see Adverse Reactions (6.1)]. The use of linagliptin in combination with insulin in subjects with severe renal impairment was associated with a higher rate of hypoglycemia [see Adverse Reactions (6.1)]. Therefore, a lower dose of the insulin secretagogue or insulin may be required to reduce the risk of hypoglycemia when used in combination with JENTADUETO [see Dosage and Administration (2.2)].

Metformin

Hypoglycemia does not occur in patients receiving metformin alone under usual circumstances of use, but could occur when caloric intake is deficient, when strenuous exercise is not compensated by caloric supplementation, or during concomitant use with other glucose-lowering agents (such as SUs and insulin) or ethanol. Elderly, debilitated, or malnourished patients, and those with adrenal or pituitary insufficiency or alcohol intoxication are particularly susceptible to hypoglycemic effects. Hypoglycemia may be difficult to recognize in the elderly, and in people who are taking β-adrenergic blocking drugs.

5.6 Hypersensitivity Reactions

There have been postmarketing reports of serious hypersensitivity reactions in patients treated with linagliptin (one of the components of JENTADUETO). These reactions include anaphylaxis, angioedema, and exfoliative skin conditions. Onset of these reactions occurred within the first 3 months after initiation of treatment with linagliptin, with some reports occurring after the first dose. If a serious hypersensitivity reaction is suspected, discontinue JENTADUETO, assess for other potential causes for the event, and institute alternative treatment for diabetes.

Angioedema has also been reported with other dipeptidyl peptidase-4 (DPP-4) inhibitors. Use caution in a patient with a history of angioedema to another DPP-4 inhibitor because it is unknown whether such patients will be predisposed to angioedema with JENTADUETO.

5.7 Vitamin B12 Levels

In controlled, 29-week clinical trials of metformin, a decrease to subnormal levels of previously normal serum vitamin B12 levels, without clinical manifestations, was observed in approximately 7% of metformin-treated patients. Such decrease, possibly due to interference with B12 absorption from the B12-intrinsic factor complex, is, however, very rarely associated with anemia or neurologic manifestations due to the short duration (<1 year) of the clinical trials. This risk may be more relevant to patients receiving long-term treatment with metformin, and adverse hematologic and neurologic reactions have been reported postmarketing. The decrease in vitamin B12 levels appears to be rapidly reversible with discontinuation of metformin or vitamin B12 supplementation. Measurement of hematologic parameters on an annual basis is advised in patients on JENTADUETO and any apparent abnormalities should be appropriately investigated and managed. Certain individuals (those with inadequate vitamin B12 or calcium intake or absorption) appear to be predisposed to developing subnormal vitamin B12 levels. In these patients, routine serum vitamin B12 measurement at 2- to 3-year intervals may be useful.

5.8 Alcohol Intake

Alcohol is known to potentiate the effect of metformin on lactate metabolism. Patients, therefore, should be warned against excessive alcohol intake while receiving JENTADUETO [see Warnings and Precautions (5.1)].

5.9 Hypoxic States

Cardiovascular collapse (shock) from whatever cause (e.g., acute congestive heart failure, acute myocardial infarction, and other conditions characterized by hypoxemia) have been associated with lactic acidosis and may also cause prerenal azotemia. When such events occur in patients on JENTADUETO therapy, the drug should be promptly discontinued [see Warnings and Precautions (5.1)].

5.10 Macrovascular Outcomes

There have been no clinical studies establishing conclusive evidence of macrovascular risk reduction with linagliptin or metformin or any other antidiabetic drug.

6 ADVERSE REACTIONS

6.1 Clinical Trials Experience

Because clinical trials are conducted under widely varying conditions, adverse reaction rates observed in the clinical trials of a drug cannot be directly compared to rates in the clinical trials of another drug and may not reflect the rates observed in practice.

Linagliptin/Metformin

The safety of concomitantly administered linagliptin (daily dose 5 mg) and metformin (mean daily dose of approximately 1800 mg) has been evaluated in 2816 patients with type 2 diabetes mellitus treated for ≥12 weeks in clinical trials.

Three placebo-controlled studies with linagliptin + metformin were conducted: 2 studies were 24 weeks in duration, 1 study was 12 weeks in duration. In the 3 placebo-controlled clinical studies, adverse events which occurred in ≥5% of patients receiving linagliptin + metformin (n=875) and were more common than in patients given placebo + metformin (n=539) included nasopharyngitis (5.7% vs 4.3%).

In a 24-week factorial design study, adverse events reported in ≥5% of patients receiving linagliptin + metformin and were more common than in patients given placebo are shown in Table 1.

Table 1 Adverse Reactions Reported in ≥5% of Patients Treated with Linagliptin + Metformin and Greater than with Placebo in a 24-week Factorial-Design Study
 | Placebo n=72 | Linagliptin Monotherapy n=142 | Metformin Monotherapy n=291 | Combination of Linagliptin with Metformin n=286
 | n (%) | n (%) | n (%) | n (%)
Nasopharyngitis | 1 (1.4) | 8 (5.6) | 8 (2.7) | 18 (6.3)
Diarrhea | 2 (2.8) | 5 (3.5) | 11 (3.8) | 18 (6.3)

Other adverse reactions reported in clinical studies with treatment of linagliptin + metformin were hypersensitivity (e.g., urticaria, angioedema, or bronchial hyperreactivity), cough, decreased appetite, nausea, vomiting, pruritus, and pancreatitis.

Linagliptin

Adverse reactions reported in ≥2% of patients treated with linagliptin 5 mg and more commonly than in patients treated with placebo included: nasopharyngitis (7.0% vs 6.1%), diarrhea (3.3% vs 3.0%), and cough (2.1% vs 1.4%).

Rates for other adverse reactions for linagliptin 5 mg vs placebo when linagliptin was used in combination with specific anti-diabetic agents were: urinary tract infection (3.1% vs 0%) and hypertriglyceridemia (2.4% vs 0%) when linagliptin was used as add-on to sulfonylurea; hyperlipidemia (2.7% vs 0.8%) and weight increased (2.3% vs 0.8%) when linagliptin was used as add-on to pioglitazone; and constipation (2.1% vs 1%) when linagliptin was used as add-on to basal insulin therapy.

Other adverse reactions reported in clinical studies with treatment of linagliptin monotherapy were hypersensitivity (e.g., urticaria, angioedema, localized skin exfoliation, or bronchial hyperreactivity) and myalgia. In the clinical trial program, pancreatitis was reported in 15.2 cases per 10,000 patient year exposure while being treated with linagliptin compared with 3.7 cases per 10,000 patient year exposure while being treated with comparator (placebo and active comparator, sulfonylurea). Three additional cases of pancreatitis were reported following the last administered dose of linagliptin.

Metformin

The most common adverse reactions due to initiation of metformin are diarrhea, nausea/vomiting, flatulence, asthenia, indigestion, abdominal discomfort, and headache.

Long-term treatment with metformin has been associated with a decrease in vitamin B12 absorption which may very rarely result in clinically significant vitamin B12 deficiency (e.g., megaloblastic anemia) [see Warnings and Precautions (5.5)].

Hypoglycemia
Linagliptin/Metformin

In a 24-week factorial design study, hypoglycemia was reported in 4 (1.4%) of 286 subjects treated with linagliptin + metformin, 6 (2.1%) of 291 subjects treated with metformin, and 1 (1.4%) of 72 subjects treated with placebo. When linagliptin was administered in combination with metformin and a sulfonylurea, 181 (22.9%) of 792 patients reported hypoglycemia compared with 39 (14.8%) of 263 patients administered placebo in combination with metformin and sulfonylurea. Adverse reactions of hypoglycemia were based on all reports of hypoglycemia. A concurrent glucose measurement was not required or was normal in some patients. Therefore, it is not possible to conclusively determine that all these reports reflect true hypoglycemia.

Linagliptin

In the study of patients receiving linagliptin as add-on therapy to a stable dose of insulin for up to 52 weeks (n=1261), no significant difference in the incidence of investigator reported hypoglycemia, defined as all symptomatic or asymptomatic episodes with a self-measured blood glucose ≤70 mg/dL, was noted between the linagliptin- (31.4%) and placebo- (32.9%) treated groups.

Use in Renal Impairment

Linagliptin was compared to placebo as add-on to pre-existing antidiabetic therapy over 52 weeks in 133 patients with severe renal impairment (estimated GFR <30 mL/min). For the initial 12 weeks of the study, background antidiabetic therapy was kept stable and included insulin, sulfonylurea, glinides, and pioglitazone. For the remainder of the trial, dose adjustments in antidiabetic background therapy were allowed.

In general, the incidence of adverse events including severe hypoglycemia was similar to those reported in other linagliptin trials. The observed incidence of hypoglycemia was higher (linagliptin, 63% compared to placebo, 49%) due to an increase in asymptomatic hypoglycemic events especially during the first 12 weeks when background glycemic therapies were kept stable. Ten linagliptin-treated patients (15%) and 11 placebo-treated patients (17%) reported at least one episode of confirmed symptomatic hypoglycemia (accompanying finger stick glucose ≤54 mg/dL). During the same time period, severe hypoglycemic events, defined as an event requiring the assistance of another person to actively administer carbohydrate, glucagon or other resuscitative actions, were reported in 3 (4.4%) linagliptin-treated patients and 3 (4.6%) placebo-treated patients. Events that were considered life-threatening or required hospitalization were reported in 2 (2.9%) patients on linagliptin and 1 (1.5%) patient on placebo.

Renal function as measured by mean eGFR and creatinine clearance did not change over 52 weeks’ treatment compared to placebo.

Laboratory Tests

Changes in laboratory findings were similar in patients treated with linagliptin + metformin compared to patients treated with placebo + metformin. Changes in laboratory values that occurred more frequently in the linagliptin + metformin group and ≥1% more than in the placebo group were not detected.

No clinically meaningful changes in vital signs were observed in patients treated with linagliptin.

6.2 Postmarketing Experience

The following adverse reactions have been identified during postapproval use of linagliptin. Because these reactions are reported voluntarily from a population of uncertain size, it is generally not possible to reliably estimate their frequency or establish a causal relationship to drug exposure.

- Acute pancreatitis, including fatal pancreatitis [see Indications and Usage (1.2) and Warnings and Precautions (5.2)]
- Hypersensitivity reactions including anaphylaxis, angioedema, and exfoliative skin conditions [see Warnings and Precautions (5.6)]
- Rash

7 DRUG INTERACTIONS

7.1 Drug Interactions with Metformin

Cationic Drugs

Cationic drugs (e.g., amiloride, digoxin, morphine, procainamide, quinidine, quinine, ranitidine, triamterene, trimethoprim, or vancomycin) that are eliminated by renal tubular secretion theoretically have the potential for interaction with metformin by competing for common renal tubular transport systems. Although such interactions remain theoretical (except for cimetidine), careful patient monitoring and dose adjustment of JENTADUETO and/or the interfering drug is recommended in patients who are taking cationic medications that are excreted via the proximal renal tubular secretory system [see Warnings and Precautions (5.3) and Clinical Pharmacology (12.3)].

Carbonic Anhydrase Inhibitors

Topiramate or other carbonic anhydrase inhibitors (e.g., zonisamide, acetazolamide or dichlorphenamide) frequently decrease serum bicarbonate and induce non-anion gap, hyperchloremic metabolic acidosis. Concomitant use of these drugs may induce metabolic acidosis. Use these drugs with caution in patients treated with JENTADUETO, as the risk of lactic acidosis may increase [see Warnings and Precautions (5.1) and Clinical Pharmacology (12.3)].

7.2 Drug Interactions with Linagliptin

Inducers of P-glycoprotein and CYP3A4 Enzymes

Rifampin decreased linagliptin exposure, suggesting that the efficacy of linagliptin may be reduced when administered in combination with a strong P-gp inducer or CYP 3A4 inducer. As JENTADUETO is a fixed-dose combination of linagliptin and metformin, use of alternative treatments (not containing linagliptin) is strongly recommended when concomitant treatment with a strong P-gp or CYP 3A4 inducer is necessary [see Clinical Pharmacology (12.3)].

7.3 Drugs Affecting Glycemic Control

Certain drugs tend to produce hyperglycemia and may lead to loss of glycemic control. These drugs include the thiazides and other diuretics, corticosteroids, phenothiazines, thyroid products, estrogens, oral contraceptives, phenytoin, nicotinic acid, sympathomimetics, calcium channel blocking drugs, and isoniazid. When such drugs are administered to a patient receiving JENTADUETO, the patient should be closely observed to maintain adequate glycemic control [see Clinical Pharmacology (12.3)]. When such drugs are withdrawn from a patient receiving JENTADUETO, the patient should be observed closely for hypoglycemia.

8 USE IN SPECIFIC POPULATIONS

8.1 Pregnancy

Pregnancy Category B

JENTADUETO

There are no adequate and well controlled studies in pregnant women with JENTADUETO or its individual components, and some clinical data is available for metformin which indicate that the risk for major malformations was not increased when metformin is taken during the first trimester in pregnancy. In addition, metformin was not associated with increased perinatal complications. Nevertheless, because these clinical data cannot rule out the possibility of harm, JENTADUETO should be used during pregnancy only if clearly needed.

JENTADUETO was not teratogenic when administered to Wistar Han rats during the period of organogenesis at doses similar to clinical exposure. At higher maternally toxic doses (9 and 23 times the clinical dose based on exposure), the metformin component of the combination was associated with an increased incidence of fetal rib and scapula malformations.

Linagliptin

Linagliptin was not teratogenic when administered to pregnant Wistar Han rats and Himalayan rabbits during the period of organogenesis at doses up to 240 mg/kg and 150 mg/kg, respectively. These doses represent approximately 943 times the clinical dose in rats and 1943 times the clinical dose in rabbits, based on exposure. No functional, behavioral, or reproductive toxicity was observed in offspring of female Wistar Han rats when administered linagliptin from gestation day 6 to lactation day 21 at a dose 49 times the maximum recommended human dose, based on exposure.

Linagliptin crosses the placenta into the fetus following oral dosing in pregnant rats and rabbits.

Metformin Hydrochloride

Metformin has been studied for embryo-fetal effects in 2 rat strains and in rabbits. Metformin was not teratogenic in Sprague Dawley rats up to 600 mg/kg or in Wistar Han rats up to 200 mg/kg (2-3 times the clinical dose based on body surface area or exposure, respectively). At higher maternally toxic doses (9 and 23 times the clinical dose based on exposure), an increased incidence of rib and scapula skeletal malformations was observed in the Wistar Han strain. Metformin was not teratogenic in rabbits at doses up to 140 mg/kg (similar to clinical dose based on body surface area).

Metformin administered to female Sprague Dawley rats from gestation day 6 to lactation day 21 up to 600 mg/kg/day (2 times the maximum clinical dose based on body surface area) had no effect on prenatal or postnatal development of offspring.

Metformin crosses the placenta into the fetus in rats and humans.

8.3 Nursing Mothers

No studies in lactating animals have been conducted with the combined components of JENTADUETO. In studies performed with the individual components, both linagliptin and metformin were secreted in the milk of lactating rats. It is not known whether linagliptin is excreted in human milk. Metformin is excreted in human milk in low concentrations. Because the potential for hypoglycemia in nursing infants may exist, a decision should be made whether to discontinue nursing or to discontinue the drug, taking into account the importance of the drug to the mother.

8.4 Pediatric Use

Safety and effectiveness of JENTADUETO in pediatric patients under 18 years of age have not been established.

8.5 Geriatric Use

Linagliptin is minimally excreted by the kidney; however, metformin is substantially excreted by the kidney. Considering that aging can be associated with reduced renal function, JENTADUETO should be used with caution as age increases [see Warnings and Precautions (5.1, 5.3) and Clinical Pharmacology (12.3)].

Linagliptin

There were 4040 type 2 diabetes patients treated with linagliptin 5 mg from 15 clinical trials of linagliptin; 1085 (27%) patients were 65 years and over, while 131 (3%) were 75 years and over. Of these patients, 2566 were enrolled in 12 double-blind placebo-controlled studies; 591 (23%) were 65 years and over, while 82 (3%) were 75 years and over. No overall differences in safety or effectiveness were observed between patients 65 years and over and younger patients. Therefore, no dose adjustment is recommended in the elderly population. While clinical studies of linagliptin have not identified differences in response between the elderly and younger patients, greater sensitivity of some older individuals cannot be ruled out.

Metformin

Controlled clinical studies of metformin did not include sufficient numbers of elderly patients to determine whether they respond differently from younger patients, although other reported clinical experience has not identified differences in responses between the elderly and young patients. The initial and maintenance dosing of metformin should be conservative in patients with advanced age, due to the potential for decreased renal function in this population. Any dose adjustment should be based on a careful assessment of renal function [see Contraindications (4), Warnings and Precautions (5.3), and Clinical Pharmacology (12.3)].

10 OVERDOSAGE

In the event of an overdose with JENTADUETO, contact the Poison Control Center. Employ the usual supportive measures (e.g., remove unabsorbed material from the gastrointestinal tract, employ clinical monitoring, and institute supportive treatment) as dictated by the patient’s clinical status. Removal of linagliptin by hemodialysis or peritoneal dialysis is unlikely. However, metformin is dialyzable with a clearance of up to 170 mL/min under good hemodynamic conditions. Therefore, hemodialysis may be useful partly for removal of accumulated metformin from patients in whom JENTADUETO overdosage is suspected.

Linagliptin

During controlled clinical trials in healthy subjects, with single doses of up to 600 mg of linagliptin (equivalent to 120 times the recommended daily dose), there were no dose-related clinical adverse drug reactions. There is no experience with doses above 600 mg in humans.

Metformin

Overdose of metformin has occurred, including ingestion of amounts greater than 50 grams. Hypoglycemia was reported in approximately 10% of cases, but no causal association with metformin has been established. Lactic acidosis has been reported in approximately 32% of metformin overdose cases [see Boxed Warning and Warnings and Precautions (5.1)].

11 DESCRIPTION

JENTADUETO tablets contain 2 oral antihyperglycemic drugs used in the management of type 2 diabetes mellitus: linagliptin and metformin hydrochloride.

Linagliptin

Linagliptin is an orally-active inhibitor of the dipeptidyl peptidase-4 (DPP-4) enzyme.

Linagliptin is described chemically as 1H-Purine-2,6-dione, 8-[(3R)-3-amino-1-piperidinyl]-7-(2-butyn-1-yl)-3,7-dihydro-3-methyl-1-[(4-methyl-2-quinazolinyl)methyl]-

The empirical formula is C25H28N8O2 and the molecular weight is 472.54 g/mol. The structural formula is:

Linagliptin is a white to yellowish, not or only slightly hygroscopic solid substance. It is very slightly soluble in water (0.9 mg/mL). Linagliptin is soluble in methanol (ca. 60 mg/mL), sparingly soluble in ethanol (ca. 10 mg/mL), very slightly soluble in isopropanol (<1 mg/mL), and very slightly soluble in acetone (ca. 1 mg/mL).

Metformin Hydrochloride

Metformin hydrochloride (N,N-dimethylimidodicarbonimidic diamide hydrochloride) is not chemically or pharmacologically related to any other classes of oral antihyperglycemic agents. Metformin hydrochloride is a white to off-white crystalline compound with a molecular formula of C4H11N5•HCl and a molecular weight of 165.63. Metformin hydrochloride is freely soluble in water and is practically insoluble in acetone, ether, and chloroform. The pKa of metformin is 12.4. The pH of a 1% aqueous solution of metformin hydrochloride is 6.68. The structural formula is:

JENTADUETO

JENTADUETO is available for oral administration as tablets containing 2.5 mg linagliptin and 500 mg metformin hydrochloride (JENTADUETO 2.5 mg/500 mg), 850 mg metformin hydrochloride (JENTADUETO 2.5 mg/850 mg) or 1000 mg metformin hydrochloride (JENTADUETO 2.5 mg/1000 mg). Each film-coated tablet of JENTADUETO contains the following inactive ingredients: arginine, corn starch, copovidone, colloidal silicon dioxide, magnesium stearate, titanium dioxide, propylene glycol, hypromellose, talc, yellow ferric oxide (2.5 mg/500 mg; 2.5 mg/850 mg) and/or red ferric oxide (2.5 mg/850 mg; 2.5 mg/1000 mg).

12 CLINICAL PHARMACOLOGY

12.1 Mechanism of Action

JENTADUETO

JENTADUETO combines 2 antihyperglycemic agents with complementary mechanisms of action to improve glycemic control in patients with type 2 diabetes mellitus: linagliptin, a dipeptidyl peptidase-4 (DPP-4) inhibitor, and metformin, a member of the biguanide class.

Linagliptin

Linagliptin is an inhibitor of DPP-4, an enzyme that degrades the incretin hormones glucagon-like peptide-1 (GLP-1) and glucose-dependent insulinotropic polypeptide (GIP). Thus, linagliptin increases the concentrations of active incretin hormones, stimulating the release of insulin in a glucose-dependent manner and decreasing the levels of glucagon in the circulation. Both incretin hormones are involved in the physiological regulation of glucose homeostasis. Incretin hormones are secreted at a low basal level throughout the day and levels rise immediately after meal intake. GLP-1 and GIP increase insulin biosynthesis and secretion from pancreatic beta cells in the presence of normal and elevated blood glucose levels. Furthermore, GLP-1 also reduces glucagon secretion from pancreatic alpha cells, resulting in a reduction in hepatic glucose output.

Metformin

Metformin is an antihyperglycemic agent which improves glucose tolerance in patients with type 2 diabetes mellitus, lowering both basal and postprandial plasma glucose. Its pharmacologic mechanisms of action are different from other classes of oral antihyperglycemic agents. Metformin decreases hepatic glucose production, decreases intestinal absorption of glucose, and improves insulin sensitivity by increasing peripheral glucose uptake and utilization. Unlike SUs, metformin does not produce hypoglycemia in either patients with type 2 diabetes mellitus or normal subjects (except in special circumstances) [see Warnings and Precautions (5.10)] and does not cause hyperinsulinemia. With metformin therapy, insulin secretion remains unchanged while fasting insulin levels and day-long plasma insulin response may actually decrease.

12.2 Pharmacodynamics

Linagliptin

Linagliptin binds to DPP-4 in a reversible manner and increases the concentrations of incretin hormones. Linagliptin glucose-dependently increases insulin secretion and lowers glucagon secretion, thus resulting in a better regulation of the glucose homeostasis. Linagliptin binds selectively to DPP-4 and selectively inhibits DPP-4, but not DPP-8 or DPP-9 activity in vitro at concentrations approximating therapeutic exposures.

Cardiac Electrophysiology

In a randomized, placebo-controlled, active-comparator, 4-way crossover study, 36 healthy subjects were administered a single oral dose of linagliptin 5 mg, linagliptin 100 mg (20 times the recommended dose), moxifloxacin, and placebo. No increase in QTc was observed with either the recommended dose of 5 mg or the 100-mg dose. At the 100-mg dose, peak linagliptin plasma concentrations were approximately 38-fold higher than the peak concentrations following a 5-mg dose.

12.3 Pharmacokinetics

JENTADUETO

The results of a bioequivalence study in healthy subjects demonstrated that JENTADUETO (linagliptin/metformin hydrochloride) 2.5 mg/500 mg, 2.5 mg/850 mg, and 2.5 mg/1000 mg combination tablets are bioequivalent to coadministration of corresponding doses of linagliptin and metformin as individual tablets. Administration of linagliptin 2.5 mg/metformin hydrochloride 1000 mg fixed-dose combination with food resulted in no change in overall exposure of linagliptin. There was no change in metformin AUC; however, mean peak serum concentration of metformin was decreased by 18% when administered with food. A delayed time-to-peak serum concentrations by 2 hours was observed for metformin under fed conditions. These changes are not likely to be clinically significant.

Absorption

Linagliptin

The absolute bioavailability of linagliptin is approximately 30%. Following oral administration, plasma concentrations of linagliptin decline in at least a biphasic manner with a long terminal half-life (>100 hours), related to the saturable binding of linagliptin to DPP-4. However, the prolonged elimination does not contribute to the accumulation of the drug. The effective half-life for accumulation of linagliptin, as determined from oral administration of multiple doses of linagliptin 5 mg, is approximately 12 hours. After once-daily dosing, steady state plasma concentrations of linagliptin 5 mg are reached by the third dose, and Cmax and AUC increased by a factor of 1.3 at steady-state compared with the first dose. Plasma AUC of linagliptin increased in a less than dose-proportional manner in the dose range of 1 to 10 mg. The pharmacokinetics of linagliptin is similar in healthy subjects and in patients with type 2 diabetes.

Metformin

The absolute bioavailability of a metformin hydrochloride 500-mg tablet given under fasting conditions is approximately 50% to 60%. Studies using single oral doses of metformin tablets 500 mg to 1500 mg, and 850 mg to 2550 mg, indicate that there is a lack of dose proportionality with increasing doses, which is due to decreased absorption rather than an alteration in elimination.

Distribution

Linagliptin

The mean apparent volume of distribution at steady state following a single intravenous dose of linagliptin 5 mg to healthy subjects is approximately 1110 L, indicating that linagliptin extensively distributes to the tissues. Plasma protein binding of linagliptin is concentration-dependent decreasing from about 99% at 1 nmol/L to 75% to 89% at ≥30 nmol/L, reflecting saturation of binding to DPP-4 with increasing concentration of linagliptin. At high concentrations, where DPP-4 is fully saturated, 70% to 80% of linagliptin remains bound to plasma proteins and 20% to 30% is unbound in plasma. Plasma binding is not altered in patients with renal or hepatic impairment.

Metformin

The apparent volume of distribution (V/F) of metformin following single oral doses of immediate-release metformin hydrochloride tablets 850 mg averaged 654±358 L. Metformin is negligibly bound to plasma proteins, in contrast to SUs, which are more than 90% protein bound. Metformin partitions into erythrocytes, most likely as a function of time. At usual clinical doses and dosing schedules of metformin tablets, steady-state plasma concentrations of metformin are reached within 24 to 48 hours and are generally <1 mcg/mL. During controlled clinical trials of metformin, maximum metformin plasma levels did not exceed 5 mcg/mL, even at maximum doses.

Metabolism

Linagliptin

Following oral administration, the majority (about 90%) of linagliptin is excreted unchanged, indicating that metabolism represents a minor elimination pathway. A small fraction of absorbed linagliptin is metabolized to a pharmacologically inactive metabolite, which shows a steady-state exposure of 13.3% relative to linagliptin.

Metformin

Intravenous single-dose studies in normal subjects demonstrate that metformin is excreted unchanged in the urine and does not undergo hepatic metabolism (no metabolites have been identified in humans) nor biliary excretion.

Excretion

Linagliptin

Following administration of an oral [^14C]linagliptin dose to healthy subjects, approximately 85% of the administered radioactivity was eliminated via the enterohepatic system (80%) or urine (5%) within 4 days of dosing. Renal clearance at steady state was approximately 70 mL/min.

Metformin

Renal clearance is approximately 3.5 times greater than creatinine clearance, which indicates that tubular secretion is the major route of metformin elimination. Following oral administration, approximately 90% of the absorbed drug is eliminated via the renal route within the first 24 hours, with a plasma elimination half-life of approximately 6.2 hours. In blood, the elimination half-life is approximately 17.6 hours, suggesting that the erythrocyte mass may be a compartment of distribution.

Specific Populations

Renal Impairment

JENTADUETO: Studies characterizing the pharmacokinetics of linagliptin and metformin after administration of JENTADUETO in renally impaired patients have not been performed. Since metformin is contraindicated in patients with renal impairment, use of JENTADUETO is also contraindicated in patients with renal impairment (e.g., serum creatinine ≥1.5 mg/dL [males] or ≥1.4 mg/dL [females], or abnormal creatinine clearance) [see Contraindications (4) and Warnings and Precautions (5.3)].

Linagliptin: Under steady-state conditions, linagliptin exposure in patients with mild renal impairment was comparable to healthy subjects. In patients with moderate renal impairment under steady-state conditions, mean exposure of linagliptin increased (AUCτ,ss by 71% and Cmax by 46%) compared with healthy subjects. This increase was not associated with a prolonged accumulation half-life, terminal half-life, or an increased accumulation factor. Renal excretion of linagliptin was below 5% of the administered dose and was not affected by decreased renal function.

Patients with type 2 diabetes mellitus and severe renal impairment showed steady-state exposure approximately 40% higher than that of patients with type 2 diabetes mellitus and normal renal function (increase in AUC by 42% and Cmax by 35%). For both type 2 diabetes mellitus groups, renal excretion was below 7% of the administered dose.

Metformin: In patients with decreased renal function (based on measured creatinine clearance), the plasma and blood half-life of metformin is prolonged and the renal clearance is decreased in proportion to the decrease in creatinine clearance [see Contraindications (4) and Warnings and Precautions (5.3)].

Hepatic Impairment

JENTADUETO: Studies characterizing the pharmacokinetics of linagliptin and metformin after administration of JENTADUETO in hepatically impaired patients have not been performed. However, use of metformin alone in patients with hepatic impairment has been associated with some cases of lactic acidosis. Therefore, use of JENTADUETO is not recommended in patients with hepatic impairment [see Warnings and Precautions (5.4)].

Linagliptin: In patients with mild hepatic impairment (Child-Pugh class A) steady-state exposure (AUCτ,ss) of linagliptin was approximately 25% lower and Cmax,ss was approximately 36% lower than in healthy subjects. In patients with moderate hepatic impairment (Child-Pugh class B), AUCss of linagliptin was about 14% lower and Cmax,ss was approximately 8% lower than in healthy subjects. Patients with severe hepatic impairment (Child-Pugh class C) had comparable exposure of linagliptin in terms of AUC0-24 and approximately 23% lower Cmax compared with healthy subjects. Reductions in the pharmacokinetic parameters seen in patients with hepatic impairment did not result in reductions in DPP-4 inhibition.

Metformin hydrochloride: No pharmacokinetic studies of metformin have been conducted in patients with hepatic impairment.

Body Mass Index (BMI)/Weight

Linagliptin: BMI/Weight had no clinically meaningful effect on the pharmacokinetics of linagliptin based on a population pharmacokinetic analysis.

Gender

Linagliptin: Gender had no clinically meaningful effect on the pharmacokinetics of linagliptin based on a population pharmacokinetic analysis.

Metformin hydrochloride: Metformin pharmacokinetic parameters did not differ significantly between normal subjects and patients with type 2 diabetes mellitus when analyzed according to gender. Similarly, in controlled clinical studies in patients with type 2 diabetes mellitus, the antihyperglycemic effect of metformin was comparable in males and females.

Geriatric

JENTADUETO: Studies characterizing the pharmacokinetics of linagliptin and metformin after administration of JENTADUETO in geriatric patients have not been performed. Based on the metformin component, JENTADUETO treatment should not be initiated in patients ≥80 years of age unless measurement of creatinine clearance demonstrates that renal function is not reduced [see Warnings and Precautions (5.1, 5.3) and Use in Specific Populations (8.5)].

Linagliptin: Age did not have a clinically meaningful impact on the pharmacokinetics of linagliptin based on a population pharmacokinetic analysis.

Metformin hydrochloride: Limited data from controlled pharmacokinetic studies of metformin in healthy elderly subjects suggest that total plasma clearance of metformin is decreased, the half-life is prolonged, and Cmax is increased, compared with healthy young subjects. From these data, it appears that the change in metformin pharmacokinetics with aging is primarily accounted for by a change in renal function.

Pediatric

Studies characterizing the pharmacokinetics of linagliptin and metformin after administration of JENTADUETO in pediatric patients have not yet been performed.

Race

Linagliptin: Race had no clinically meaningful effect on the pharmacokinetics of linagliptin based on available pharmacokinetic data, including subjects of White, Hispanic, Black, and Asian racial groups.

Metformin hydrochloride: No studies of metformin pharmacokinetic parameters according to race have been performed. In controlled clinical studies of metformin in patients with type 2 diabetes mellitus, the antihyperglycemic effect was comparable in Caucasians (n=249), Blacks (n=51), and Hispanics (n=24).

Drug Interactions

Pharmacokinetic drug interaction studies with JENTADUETO have not been performed; however, such studies have been conducted with the individual components of JENTADUETO (linagliptin and metformin hydrochloride).

Linagliptin

In vitro Assessment of Drug Interactions

Linagliptin is a weak to moderate inhibitor of CYP isozyme CYP3A4, but does not inhibit other CYP isozymes and is not an inducer of CYP isozymes, including CYP1A2, 2A6, 2B6, 2C8, 2C9, 2C19, 2D6, 2E1, and 4A11.

Linagliptin is a P-glycoprotein (P-gp) substrate, and inhibits P-gp mediated transport of digoxin at high concentrations. Based on these results and in vivo drug interaction studies, linagliptin is considered unlikely to cause interactions with other P-gp substrates at therapeutic concentrations.

In vivo Assessment of Drug Interactions

Strong inducers of CYP3A4 or P-gp (e.g., rifampin) decrease exposure to linagliptin to subtherapeutic and likely ineffective concentrations. For patients requiring use of such drugs, an alternative to linagliptin is strongly recommended. In vivo studies indicated evidence of a low propensity for causing drug interactions with substrates of CYP3A4, CYP2C9, CYP2C8, P-gp, and OCT. No dose adjustment of linagliptin is recommended based on results of the described pharmacokinetic studies.

Table 2 Effect of Coadministered Drugs on Systemic Exposure of Linagliptin
Coadministered Drug | Dosing of Coadministered Drug* | Dosing of Linagliptin* | Geometric Mean Ratio (ratio with/without coadministered drug) No effect=1.0
Coadministered Drug | Dosing of Coadministered Drug* | Dosing of Linagliptin* | AUC† | Cmax
No dosing adjustments required for linagliptin when given with the following coadministered drugs:
Metformin | 850 mg TID | 10 mg QD | 1.20 | 1.03
Glyburide | 1.75 mg# | 5 mg QD | 1.02 | 1.01
Pioglitazone | 45 mg QD | 10 mg QD | 1.13 | 1.07
Ritonavir | 200 mg BID | 5 mg# | 2.01 | 2.96
The efficacy of JENTADUETO may be reduced when administered in combination with strong inducers of CYP3A4 or P-gp (e.g., rifampin). Use of alternative treatments is strongly recommended [see Drug Interactions (7.2)].
Rifampin | 600 mg QD | 5 mg QD | 0.60 | 0.56
*Multiple dose (steady state) unless otherwise noted
# Single dose
†AUC = AUC(0 to 24 hours) for single-dose treatments and AUC = AUC(TAU) for multiple-dose treatments
QD = once daily
BID = twice daily
TID = three times daily

Table 3 Effect of Linagliptin on Systemic Exposure of Coadministered Drugs
Coadministered Drug | Dosing of Coadministered Drug* | Dosing of Linagliptin* | Geometric Mean Ratio (ratio with/without coadministered drug) No effect=1.0
Coadministered Drug | Dosing of Coadministered Drug* | Dosing of Linagliptin* |  | AUC† | Cmax
No dosing adjustments required for the following coadministered drugs:
Metformin | 850 mg TID | 10 mg QD | metformin | 1.01 | 0.89
Glyburide | 1.75 mg# | 5 mg QD | glyburide | 0.86 | 0.86
Pioglitazone | 45 mg QD | 10 mg QD | pioglitazone metabolite M-III metabolite M-IV | 0.94 0.98 1.04 | 0.86 0.96 1.05
Digoxin | 0.25 mg QD | 5 mg QD | digoxin | 1.02 | 0.94
Simvastatin | 40 mg QD | 10 mg QD | simvastatin simvastatin acid | 1.34 1.33 | 1.10 1.21
Warfarin | 10 mg# | 5 mg QD | R-warfarin S-warfarin INR PT | 0.99 1.03 0.93** 1.03** | 1.00 1.01 1.04** 1.15**
Ethinylestradiol and levonorgestrel | ethinylestradiol 0.03 mg and levonorgestrel 0.150 mg QD | 5 mg QD | ethinylestradiol levonorgestrel | 1.01 1.09 | 1.08 1.13
* Multiple dose (steady state) unless otherwise noted
# Single dose
†AUC = AUC(INF) for single-dose treatments and AUC = AUC(TAU) for multiple-dose treatments
**AUC=AUC(0-168) and Cmax=Emax for pharmacodynamic end points
INR = International Normalized Ratio
PT = Prothrombin Time
QD = once daily
TID = three times daily

Metformin hydrochloride

Table 4 Effect of Coadministered Drug on Plasma Metformin Systemic Exposure
Coadministered Drug | Dosing of Coadministered Drug* | Dose of Metformin* | Geometric Mean Ratio (ratio with/without coadministered drug) No effect=1.0
Coadministered Drug | Dosing of Coadministered Drug* | Dose of Metformin* |  | AUC† | Cmax
No dosing adjustments required for the following coadministered drugs:
Furosemide | 40 mg | 850 mg | metformin | 1.09‡ | 1.22‡
Nifedipine | 10 mg | 850 mg | metformin | 1.16 | 1.21
Propranolol | 40 mg | 850 mg | metformin | 0.90 | 0.94
Ibuprofen | 400 mg | 850 mg | metformin | 1.05‡ | 1.07‡
Cationic drugs eliminated by renal tubular secretion may reduce metformin elimination: use with caution [see Warnings and Precautions (5.3) and Drug Interactions (7.1)].
Cimetidine | 400 mg | 850 mg | metformin | 1.40 | 1.61
Carbonic anhydrase inhibitors may cause metabolic acidosis: use with caution [see Warnings and Precautions (5.1) and Drug Interactions (7.1)].
Topiramate** | 100 mg | 500 mg | metformin | 1.25 | 1.17
* All metformin and coadministered drugs were given as single doses
† AUC = AUC(INF)
‡ Ratio of arithmetic means
**At steady state with topiramate 100 mg every 12 hours and metformin 500 mg every 12 hours; AUC = AUC0-12h

Table 5 Effect of Metformin on Coadministered Drug Systemic Exposure
Coadministered Drug | Dosing of Coadministered Drug* | Dose of Metformin* | Geometric Mean Ratio (ratio with/without metformin) No effect=1.0
Coadministered Drug | Dosing of Coadministered Drug* | Dose of Metformin* |  | AUC† | Cmax
No dosing adjustments required for the following coadministered drugs:
Glyburide | 5 mg | 500 mg§ | glyburide | 0.78‡ | 0.63‡
Furosemide | 40 mg | 850 mg | furosemide | 0.87‡ | 0.69‡
Nifedipine | 10 mg | 850 mg | nifedipine | 1.10§ | 1.08
Propranolol | 40 mg | 850 mg | propranolol | 1.01§ | 0.94
Ibuprofen | 400 mg | 850 mg | ibuprofen | 0.97¶ | 1.01¶
* All metformin and coadministered drugs were given as single doses
† AUC = AUC(INF) unless otherwise noted
‡ Ratio of arithmetic means, p-value of difference <0.05
§ AUC(0-24 hr) reported
¶ Ratio of arithmetic means

13 NONCLINICAL TOXICOLOGY

13.1 Carcinogenesis, Mutagenesis, Impairment of Fertility

JENTADUETO

No animal studies have been conducted with the combined products in JENTADUETO to evaluate carcinogenesis, mutagenesis, or impairment of fertility. General toxicity studies in rats up to 13 weeks were performed with JENTADUETO.

The following data are based on the findings in studies with linagliptin and metformin individually.

Linagliptin

Linagliptin did not increase the incidence of tumors in male and female rats in a 2-year study at doses of 6, 18, and 60 mg/kg. The highest dose of 60 mg/kg is approximately 418 times the clinical dose of 5 mg/day based on AUC exposure. Linagliptin did not increase the incidence of tumors in mice in a 2-year study at doses up to 80 mg/kg (males) and 25 mg/kg (females), or approximately 35 and 270 times the clinical dose based on AUC exposure. Higher doses of linagliptin in female mice (80 mg/kg) increased the incidence of lymphoma at approximately 215 times the clinical dose based on AUC exposure.

Linagliptin was not mutagenic or clastogenic with or without metabolic activation in the Ames bacterial mutagenicity assay, a chromosomal aberration test in human lymphocytes, and an in vivo micronucleus assay.

In fertility studies in rats, linagliptin had no adverse effects on early embryonic development, mating, fertility, or bearing live young up to the highest dose of 240 mg/kg (approximately 943 times the clinical dose based on AUC exposure).

Metformin Hydrochloride

Long-term carcinogenicity studies have been performed in rats (dosing duration of 104 weeks) and mice (dosing duration of 91 weeks) at doses up to and including 900 mg/kg/day and 1500 mg/kg/day, respectively. These doses are both approximately 4 times the maximum recommended human daily dose of 2000 mg/kg/day based on body surface area comparisons. No evidence of carcinogenicity with metformin was found in either male or female mice. Similarly, there was no tumorigenic potential observed with metformin in male rats. There was, however, an increased incidence of benign stromal uterine polyps in female rats treated with 900 mg/kg/day.

There was no evidence of a mutagenic potential of metformin in the following in vitro tests: Ames test (Salmonella typhimurium), gene mutation test (mouse lymphoma cells), or chromosomal aberrations test (human lymphocytes). Results in the in vivo mouse micronucleus test were also negative.

Fertility of male or female rats was unaffected by metformin when administered at doses as high as 600 mg/kg/day, which is approximately 2 times the MRHD based on body surface area comparisons.

14 CLINICAL STUDIES

The coadministration of linagliptin and metformin has been studied in patients with type 2 diabetes mellitus inadequately controlled on diet and exercise and in combination with sulfonylurea.

There have been no clinical efficacy studies conducted with JENTADUETO; however, bioequivalence of JENTADUETO to linagliptin and metformin coadministered as individual tablets was demonstrated in healthy subjects.

14.1 Initial Combination Therapy with Linagliptin and Metformin

A total of 791 patients with type 2 diabetes mellitus and inadequate glycemic control on diet and exercise participated in the 24-week, randomized, double-blind, portion of this placebo-controlled factorial study designed to assess the efficacy of linagliptin as initial therapy with metformin. Patients on an antihyperglycemic agent (52%) underwent a drug washout period of 4 weeks’ duration. After the washout period and after completing a 2-week single-blind placebo run-in period, patients with inadequate glycemic control (A1C ≥7.0% to ≤10.5%) were randomized. Patients with inadequate glycemic control (A1C ≥7.5% to <11.0%) not on antihyperglycemic agents at study entry (48%) immediately entered the 2-week single-blind placebo run-in period and then were randomized. Randomization was stratified by baseline A1C (<8.5% vs ≥8.5%) and use of a prior oral antidiabetic drug (none vs monotherapy). Patients were randomized in a 1:2:2:2:2:2 ratio to either placebo or one of 5 active-treatment arms. Approximately equal numbers of patients were randomized to receive initial therapy with 5 mg of linagliptin once daily, 500 mg or 1000 mg of metformin twice daily, or 2.5 mg of linagliptin twice daily in combination with 500 mg or 1000 mg of metformin twice daily. Patients who failed to meet specific glycemic goals during the study were treated with sulfonylurea, thiazolidinedione, or insulin rescue therapy.

Initial therapy with the combination of linagliptin and metformin provided significant improvements in A1C, and fasting plasma glucose (FPG) compared to placebo, to metformin alone, and to linagliptin alone (Table 6, Figure 1). The adjusted mean treatment difference in A1C from baseline to week 24 (LOCF) was -0.5% (95% CI -0.7, -0.3; p<0.0001) for linagliptin 2.5 mg/metformin 1000 mg twice daily compared to metformin 1000 mg twice daily; -1.1% (95% CI -1.4, -0.9; p<0.0001) for linagliptin 2.5 mg/metformin 1000 mg twice daily compared to linagliptin 5 mg once daily; -0.6% (95% CI -0.8, -0.4; p<0.0001) for linagliptin 2.5 mg/metformin 500 mg twice daily compared to metformin 500 mg twice daily; and -0.8% (95% CI -1.0, -0.6; p<0.0001) for linagliptin 2.5 mg/metformin 500 mg twice daily compared to linagliptin 5 mg once daily.

Lipid effects were generally neutral. No meaningful change in body weight was noted in any of the 6 treatment groups.

Table 6 Glycemic Parameters at Final Visit (24-Week Study) for Linagliptin and Metformin, Alone and in Combination in Randomized Patients with Type 2 Diabetes Mellitus Inadequately Controlled on Diet and Exercise**
 | Placebo | Linagliptin 5 mg Once Daily* | Metformin 500 mg Twice Daily | Linagliptin 2.5 mg Twice Daily* + Metformin 500 mg Twice Daily | Metformin 1000 mg Twice Daily | Linagliptin 2.5 mg Twice Daily* + Metformin 1000 mg Twice Daily
A1C (%)
Number of patients | n=65 | n=135 | n=141 | n=137 | n=138 | n=140
Baseline (mean) | 8.7 | 8.7 | 8.7 | 8.7 | 8.5 | 8.7
Change from baseline (adjusted mean****) | 0.1 | -0.5 | -0.6 | -1.2 | -1.1 | -1.6
Difference from placebo (adjusted mean) (95% CI) | -- | -0.6 (-0.9, -0.3) | -0.8 (-1.0, -0.5) | -1.3 (-1.6, -1.1) | -1.2 (-1.5, -0.9) | -1.7 (-2.0, -1.4)
Patients [n (%)] achieving A1C <7%*** | 7 (10.8) | 14 (10.4) | 26 (18.6) | 41 (30.1) | 42 (30.7) | 74 (53.6)
Patients (%) receiving rescue medication | 29.2 | 11.1 | 13.5 | 7.3 | 8.0 | 4.3
FPG (mg/dL)
Number of patients | n=61 | n=134 | n=136 | n=135 | n=132 | n=136
Baseline (mean) | 203 | 195 | 191 | 199 | 191 | 196
Change from baseline (adjusted mean****) | 10 | -9 | -16 | -33 | -32 | -49
Difference from placebo (adjusted mean) (95% CI) | -- | -19 (-31, -6) | -26 (-38, -14) | -43 (-56, -31) | -42 (-55, -30) | -60 (-72, -47)
*Total daily dose of linagliptin is equal to 5 mg
**Full analysis population using last observation on study
***Metformin 500 mg twice daily, n=140; Linagliptin 2.5 mg twice daily + Metformin 500 twice daily, n=136; Metformin 1000 mg twice daily, n=137; Linagliptin 2.5 mg twice daily + Metformin 1000 mg twice daily, n=138.
****HbA1c: ANCOVA model included treatment and number of prior OADs as class-effects, as well as baseline HbA1c as continuous covariates. FPG: ANCOVA model included treatment and number of prior OADs as class-effects, as well as baseline HbA1c and baseline FPG as continuous covariates.

Figure 1 Adjusted Mean Change from Baseline for A1C (%) over 24 Weeks with Linagliptin and Metformin, Alone and in Combination in Patients with Type 2 Diabetes Mellitus Inadequately Controlled with Diet and Exercise - FAS completers

14.2 Initial Combination Therapy with Linagliptin and Metformin vs Linagliptin in Treatment-Naïve Patients

A total of 316 patients with type 2 diabetes diagnosed within the previous 12 months and treatment-naïve (no antidiabetic therapy for 12 weeks prior to randomization) and inadequate glycemic control (A1C ≥8.5% to ≤12.0%) participated in a 24-week, randomized, double-blind, study designed to assess the efficacy of linagliptin in combination with metformin vs linagliptin. Patients were randomized (1:1), after a 2-week run-in period, to either linagliptin 5 mg plus metformin (1500 to 2000 mg per day, n=159) or linagliptin 5 mg plus placebo, (n=157) administered once daily. Patients in the linagliptin and metformin treatment group were up-titrated to a maximum tolerated dose of metformin (1000 to 2000 mg per day) over a three-week period.

Initial therapy with the combination of linagliptin and metformin provided statistically significant improvements in A1C compared to linagliptin (Table 7). The mean difference between groups in A1C change from baseline was -0.8% with 2-sided 95% confidence interval (-1.23%, -0.45%).

Table 7 Glycemic Parameters at 24 Weeks in Study Comparing Linagliptin in Combination with Metformin to Linagliptin in Treatment-Naïve Patients*
 |  | Linagliptin 5 mg + Metformin | Linagliptin 5 mg + Placebo
A1C (%)*
 | Number of patients | n=153 | n=150
 | Baseline (mean) | 9.8 | 9.9
 | Change from baseline (adjusted mean) | -2.9 | -2
 | Difference from linagliptin (adjusted mean**) (95% CI) | -0.84† (-1.23, -0.45) | --
 | Patients [n (%)] achieving A1C <7%* | 82 (53.6) | 45 (30)
FPG (mg/dL)*
 | Number of patients | n=153 | n=150
 | Baseline (mean) | 196 | 198
 | Change from baseline (adjusted mean) | -54 | -35
 | Difference from linagliptin (adjusted mean**) (95% CI) | -18†† (-31, -5.5) | --
†p<0.0001 compared to linagliptin, ††p=0.0054 compared to linagliptin
*Full analysis set population
**A1C: MMRM model included treatment, continuous baseline A1C, baseline A1C by visit interaction, visit by treatment interaction, baseline renal impairment by treatment interaction and baseline renal impairment by treatment by visit interaction. FPG: MMRM model included treatment, continuous baseline A1C, continuous baseline FPG, baseline FPG by visit interaction, visit by treatment interaction, baseline renal impairment by treatment interaction and baseline renal impairment by treatment by visit interaction.

The adjusted mean changes for A1C (%) from baseline over time for linagliptin and metformin as compared to linagliptin alone were maintained throughout the 24 week treatment period. Using the completers analysis the respective adjusted means for A1C (%) changes from baseline for linagliptin and metformin as compared to linagliptin alone were -1.9 and -1.3 at week 6, -2.6 and -1.8 at week 12, -2.7 and -1.9 at week 18, and -2.7 and -1.9 at week 24.

Changes in body weight from baseline were not clinically significant in either treatment group.

14.3 Add-On Combination Therapy with Metformin

A total of 701 patients with type 2 diabetes participated in a 24-week, randomized, double-blind, placebo-controlled study designed to assess the efficacy of linagliptin in combination with metformin. Patients already on metformin (n=491) at a dose of at least 1500 mg per day were randomized after completing a 2-week open-label placebo run-in period. Patients on metformin and another antihyperglycemic agent (n=207) were randomized after a run-in period of approximately 6 weeks on metformin (at a dose of at least 1500 mg per day) in monotherapy. Patients were randomized to the addition of either linagliptin 5 mg or placebo, administered once daily. Patients who failed to meet specific glycemic goals during the studies were treated with glimepiride rescue.

In combination with metformin, linagliptin provided statistically significant improvements in A1C, FPG, and 2-hour PPG compared with placebo (Table 8). Rescue glycemic therapy was used in 7.8% of patients treated with linagliptin 5 mg and in 18.9% of patients treated with placebo. A similar decrease in body weight was observed for both treatment groups.

Table 8 Glycemic Parameters in Placebo-Controlled Study for Linagliptin in Combination with Metformin*
 | Linagliptin 5 mg + Metformin | Placebo + Metformin
A1C (%)
Number of patients | n=513 | n=175
Baseline (mean) | 8.1 | 8.0
Change from baseline (adjusted mean***) | -0.5 | 0.15
Difference from placebo + metformin (adjusted mean) (95% CI) | -0.6 (-0.8, -0.5) | --
Patients [n (%)] achieving A1C <7% ** | 127 (26.2) | 15 (9.2)
FPG (mg/dL)
Number of patients | n=495 | n=159
Baseline (mean) | 169 | 164
Change from baseline (adjusted mean***) | -11 | 11
Difference from placebo + metformin (adjusted mean) (95% CI) | -21 (-27, -15) | --
2-hour PPG (mg/dL)
Number of patients | n=78 | n=21
Baseline (mean) | 270 | 274
Change from baseline (adjusted mean***) | -49 | 18
Difference from placebo + metformin (adjusted mean) (95% CI) | -67 (-95, -40) | --
* Full analysis population using last observation on study
**Linagliptin 5 mg + Metformin, n=485; Placebo + Metformin, n=163.
***HbA1c: ANCOVA model included treatment and number of prior oral OADs as class-effects, as well as baseline HbA1c as continuous covariates. FPG: ANCOVA model included treatment and number of prior OADs as class-effects, as well as baseline HbA1c and baseline FPG as continuous covariates. PPG: ANCOVA model included treatment and number of prior OADs as class-effects, as well as baseline HbA1c and baseline postprandial glucose after two hours as covariate.

14.4 Active-Controlled Study vs Glimepiride in Combination with Metformin

The efficacy of linagliptin was evaluated in a 104-week double-blind, glimepiride-controlled non-inferiority study in type 2 diabetic patients with insufficient glycemic control despite metformin therapy. Patients being treated with metformin only entered a run-in period of 2 weeks’ duration, whereas patients pretreated with metformin and one additional antihyperglycemic agent entered a run-in treatment period of 6 weeks’ duration with metformin monotherapy (dose of ≥1500 mg per day) and washout of the other agent. After an additional 2-week placebo run-in period, those with inadequate glycemic control (A1C 6.5% to 10%) were randomized 1:1 to the addition of linagliptin 5 mg once daily or glimepiride. Randomization was stratified by baseline HbA1c (<8.5% vs ≥8.5%), and the previous use of antidiabetic drugs (metformin alone vs metformin plus one other OAD). Patients receiving glimepiride were given an initial dose of 1 mg/day and then electively titrated over the next 12 weeks to a maximum dose of 4 mg/day as needed to optimize glycemic control. Thereafter, the glimepiride dose was to be kept constant, except for down-titration to prevent hypoglycemia.

After 52 weeks and 104 weeks, linagliptin and glimepiride both had reductions from baseline in A1C (52 weeks: -0.4% for linagliptin, -0.6% for glimepiride; 104 weeks: -0.2% for linagliptin, -0.4% for glimepiride) from a baseline mean of 7.7% (Table 9). The mean difference between groups in A1C change from baseline was 0.2% with 2-sided 97.5% confidence interval (0.1%, 0.3%) for the intent-to-treat population using last observation carried forward. These results were consistent with the completers analysis.

Table 9 Glycemic Parameters at 52 and 104 Weeks in Study Comparing Linagliptin to Glimepiride as Add-On Therapy in Patients Inadequately Controlled on Metformin**
 | Week 52 |  | Week 104
 | Linagliptin 5 mg + Metformin | Glimepiride + Metformin (mean glimepiride dose 3 mg) | Linagliptin 5 mg + Metformin | Glimepiride + Metformin (mean glimepiride dose 3 mg)
A1C (%)
Number of patients | n=764 | n=755 | n=764 | n=755
Baseline (mean) | 7.7 | 7.7 | 7.7 | 7.7
Change from baseline (adjusted mean***) | -0.4 | -0.6 | -0.2 | -0.4
Difference from glimepiride (adjusted mean) (97.5% CI) | 0.2 (0.1, 0.3) | -- | 0.2 (0.1, 0.3) | --
FPG (mg/dL)
Number of patients | n=733 | n=725 | n=733 | n=725
Baseline (mean) | 164 | 166 | 164 | 166
Change from baseline (adjusted mean***) | -8* | -15 | -2† | -9
*p<0.0001 vs glimepiride; †p=0.0012 vs glimepiride
**Full analysis population using last observation on study
***HbA1c: ANCOVA model included treatment and number of prior OADs as class-effects, as well as baseline HbA1c as continuous covariates. FPG: ANCOVA model included treatment and number of prior OADs as class-effects, as well as baseline HbA1c and baseline FPG as continuous covariates.

Patients treated with linagliptin had a mean baseline body weight of 86 kg and were observed to have an adjusted mean decrease in body weight of 1.1 kg at 52 weeks and 1.4 kg at 104 weeks. Patients on glimepiride had a mean baseline body weight of 87 kg and were observed to have an adjusted mean increase from baseline in body weight of 1.4 kg at 52 weeks and 1.3 kg at 104 weeks (treatment difference p<0.0001 for both timepoints).

14.5 Add-On Combination Therapy with Metformin and a Sulfonylurea

A total of 1058 patients with type 2 diabetes mellitus participated in a 24-week, randomized, double-blind, placebo-controlled study designed to assess the efficacy of linagliptin in combination with a sulfonylurea and metformin. The most common sulfonylureas used by patients in the study were glimepiride (31%), glibenclamide (26%), and gliclazide (26% [not available in the United States]). Patients on a sulfonylurea and metformin were randomized to receive linagliptin 5 mg or placebo, each administered once daily. Patients who failed to meet specific glycemic goals during the study were treated with pioglitazone rescue. Glycemic end points measured included A1C and FPG.

In combination with a sulfonylurea and metformin, linagliptin provided statistically significant improvements in A1C and FPG compared with placebo (Table 10). In the entire study population (patients on linagliptin in combination with a sulfonylurea and metformin), a mean reduction from baseline relative to placebo in A1C of -0.6% and in FPG of -13 mg/dL was seen. Rescue therapy was used in 5.4% of patients treated with linagliptin 5 mg and in 13% of patients treated with placebo. Change from baseline in body weight did not differ significantly between the groups.

Table 10 Glycemic Parameters at Final Visit (24-Week Study) for Linagliptin in Combination with Metformin and Sulfonylurea*
 | Linagliptin 5 mg + Metformin + SU | Placebo + Metformin + SU
A1C (%)
Number of patients | n=778 | n=262
Baseline (mean) | 8.2 | 8.1
Change from baseline (adjusted mean***) | -0.7 | -0.1
Difference from placebo (adjusted mean) (95% CI) | -0.6 (-0.7, -0.5) | --
Patients [n (%)] achieving A1C <7%** | 217 (29.2) | 20 (8.1)
FPG (mg/dL)
Number of patients | n=739 | n=248
Baseline (mean) | 159 | 163
Change from baseline (adjusted mean***) | -5 | 8
Difference from placebo (adjusted mean) (95% CI) | -13 (-18, -7) | --
SU=sulfonylurea
*Full analysis population using last observation on study
**Linagliptin 5 mg + Metformin + SU, n=742; Placebo + Metformin + SU, n=247
***HbA1c: ANCOVA model included treatment as class-effects and baseline HbA1c as continuous covariates. FPG: ANCOVA model included treatment as class-effects, as well as baseline HbA1c and baseline FPG as continuous covariates.

14.6 Add-On Combination Therapy with Insulin

A total of 1261 patients with type 2 diabetes inadequately controlled on basal insulin alone or basal insulin in combination with oral drugs participated in a randomized, double-blind placebo-controlled trial designed to evaluate the efficacy of linagliptin as add-on therapy to basal insulin over 24 weeks. Randomization was stratified by baseline HbA1c (<8.5% vs ≥8.5%), renal function impairment status (based on baseline eGFR), and concomitant use of oral antidiabetic drugs (none, metformin only, pioglitazone only, metformin + pioglitazone). Patients with a baseline A1C of >7% and <10% were included in the study including 709 patients with renal impairment (eGFR <90 mL/min), most of whom (n=575) were categorized as mild renal impairment (eGFR 60 to <90 mL/min). Patients entered a 2-week placebo run-in period on basal insulin (e.g., insulin glargine, insulin detemir, or NPH insulin) with or without metformin and/or pioglitazone background therapy. Following the run-in period, patients with inadequate glycemic control were randomized to the addition of either 5 mg of linagliptin or placebo, administered once daily. Patients were maintained on a stable dose of insulin prior to enrollment, during the run-in period, and during the first 24 weeks of treatment. Patients who failed to meet specific glycemic goals during the double-blind treatment period were rescued by increasing background insulin dose.

Linagliptin used in combination with insulin (with or without metformin and/or pioglitazone), provided statistically significant improvements in A1C and FPG compared to placebo (Table 11) after 24 weeks of treatment. The mean total daily insulin dose at baseline was 42 units for patients treated with linagliptin and 40 units for patients treated with placebo. Background baseline diabetes therapy included use of: insulin alone (16.1%), insulin combined with metformin only (75.5%), insulin combined with metformin and pioglitazone (7.4%), and insulin combined with pioglitazone only (1%). The mean change from baseline to Week 24 in the daily dose of insulin was +1.3 IU in the placebo group and +0.6 IU in the linagliptin group. The mean change in body weight from baseline to Week 24 was similar in the two treatment groups. The rate of hypoglycemia, defined as all symptomatic or asymptomatic episodes with a self measured blood glucose was also similar in both groups (21.4% linagliptin; 22.9% placebo) in the first 24 weeks of the study.

Table 11 Glycemic Parameters in Placebo-Controlled Study for Linagliptin in Combination with Insulin*
 | Linagliptin 5 mg + Insulin | Placebo + Insulin
A1C (%)
Number of patients | n=618 | n=617
Baseline (mean) | 8.3 | 8.3
Change from baseline (adjusted mean***) | -0.6 | 0.1
Difference from placebo (adjusted mean) (95% CI) | -0.7 (-0.7, -0.6) | --
Patients [n (%)] achieving A1C <7%** | 116 (19.5) | 48 (8.1)
FPG (mg/dL)
Number of patients | n=613 | n=608
Baseline (mean) | 147 | 151
Change from baseline (adjusted mean***) | -8 | 3
Difference from placebo (adjusted mean) (95% CI) | -11 (-16, -6) | --
*Full analysis population using last observation carried forward (LOCF) method on study
**Linagliptin + Insulin, n=595; Placebo + Insulin, n=593
***HbA1c: ANCOVA model included treatment, categorical renal function impairment status and concomitant OADs as class-effects, as well as baseline HbA1c as continuous covariates. FPG: ANCOVA model included treatment, categorical renal function impairment status and concomitant OADs as class-effects, as well as baseline HbA1c and baseline FPG as continuous covariates.

The difference between treatment with linagliptin and placebo in terms of adjusted mean change from baseline in HbA1c after 24 weeks was comparable for patients with no renal impairment (eGRF ≥90 mL/min, n=539), with mild renal impairment (eGFR 60 to <90 mL/min, n=565), or with moderate renal impairment (eGFR 30 to <60 mL/min, n=124).

14.7 Renal Impairment

A total of 133 patients with type 2 diabetes participated in a 52 week, double-blind, randomized, placebo-controlled trial designed to evaluate the efficacy and safety of linagliptin in patients with both type 2 diabetes and severe chronic renal impairment. Participants with an estimated (based on the four variables modified diet in renal disease [MDRD] equation) GFR value of <30 mL/min were eligible to participate in the study. Randomization was stratified by baseline HbA1c (≤8% and >8%) and background antidiabetic therapy (insulin or any combination with insulin, SU or glinides as monotherapy and pioglitazone or any other antidiabetics excluding any other DPP-4 inhibitors). For the initial 12 weeks of the study, background antidiabetic therapy was kept stable and included insulin, sulfonylurea, glinides, and pioglitazone. For the remainder of the trial, dose adjustments in antidiabetic background therapy were allowed. At baseline in this trial, 62.5% of patients were receiving insulin alone as background diabetes therapy, and 12.5% were receiving sulfonylurea alone.

After 12 weeks of treatment, linagliptin 5 mg provided statistically significant improvement in A1C compared to placebo, with an adjusted mean change of -0.6% compared to placebo (95% confidence interval -0.9, -0.3) based on the analysis using last observation carried forward (LOCF). With adjustments in antidiabetic background therapy after the initial 12 weeks, efficacy was maintained for 52 weeks, with an adjusted mean change from baseline in A1C of -0.7% compared to placebo (95% confidence interval -1.0, -0.4) based on analysis using LOCF.

16 HOW SUPPLIED/STORAGE AND HANDLING

JENTADUETO (linagliptin and metformin hydrochloride) tablets 2.5 mg/1000 mg are supplied as follows:

Bottles of 60 (NDC 54868-6461-0)

Storage

Store at 25°C (77°F); excursions permitted to 15°-30°C (59°-86°F) [see USP Controlled Room Temperature]. Protect from exposure to high humidity. Store in a safe place out of reach of children.

17 PATIENT COUNSELING INFORMATION

Advise the patient to read the FDA-approved patient labeling (Medication Guide)

Medication Guide
Instruct patients to read the Medication Guide before starting JENTADUETO therapy and to reread each time the prescription is renewed. Instruct patients to inform their doctor if they develop any bothersome or unusual symptoms, or if any symptom persists or worsens.

Inform patients of the potential risks and benefits of JENTADUETO and of alternative modes of therapy. Also inform patients about the importance of adherence to dietary instructions, regular physical activity, periodic blood glucose monitoring and A1C testing, recognition and management of hypoglycemia and hyperglycemia, and assessment for diabetes complications. Advise patients to seek medical advice promptly during periods of stress such as fever, trauma, infection, or surgery, as medication requirements may change.

Lactic Acidosis
Inform patients of the risks of lactic acidosis due to the metformin component, its symptoms, and conditions that predispose to its development [see Warnings and Precautions (5.1)]. Advise patients to discontinue JENTADUETO immediately and to notify their doctor promptly if unexplained hyperventilation, malaise, myalgia, unusual somnolence, slow or irregular heart beat, sensation of feeling cold (especially in the extremities), or other nonspecific symptoms occur. GI symptoms are common during initiation of metformin treatment and may occur during initiation of JENTADUETO therapy; however, advise patients to consult their doctor if they develop unexplained symptoms. Although GI symptoms that occur after stabilization are unlikely to be drug related, such an occurrence of symptoms should be evaluated to determine if it may be due to metformin-induced lactic acidosis or other serious disease.

Pancreatitis
Inform patients that acute pancreatitis has been reported during postmarketing use of linagliptin. Inform patients that persistent severe abdominal pain, sometimes radiating to the back, which may or may not be accompanied by vomiting, is the hallmark symptom of acute pancreatitis. Instruct patients to discontinue JENTADUETO promptly and contact their physician if persistent severe abdominal pain occurs [see Warnings and Precautions (5.2)].

Monitoring of Renal Function
Inform patients about the importance of regular testing of renal function and hematological parameters when receiving treatment with JENTADUETO.

Instruct patients to inform their doctor that they are taking JENTADUETO prior to any surgical or radiological procedure, as temporary discontinuation of JENTADUETO may be required until renal function has been confirmed to be normal [see Warnings and Precautions (5.3)].

Hypoglycemia
Inform patients that the risk of hypoglycemia is increased when JENTADUETO is used in combination with an insulin secretagogue (e.g., sulfonylurea), and that a lower dose of the insulin secretagogue may be required to reduce the risk of hypoglycemia [see Warnings and Precautions (5.5)].

Hypersensitivity Reactions
Inform patients that serious allergic reactions, such as anaphylaxis, angioedema, and exfoliative skin conditions, have been reported during postmarketing use of linagliptin (one of the components of JENTADUETO). If symptoms of allergic reactions (such as rash, skin flaking or peeling, urticaria, swelling of the skin, or swelling of the face, lips, tongue, and throat that may cause difficulty in breathing or swallowing) occur, patients must stop taking JENTADUETO and seek medical advice promptly [see Warnings and Precautions (5.6)].

Missed Dose
Instruct patients to take JENTADUETO only as prescribed. If a dose is missed, advise patients not to double their next dose.

Alcohol Intake
Warn patients against excessive alcohol intake, either acute or chronic, while receiving JENTADUETO [see Warnings and Precautions (5.7)].

Blood Glucose and A1C Monitoring
Inform patients that response to all diabetic therapies should be monitored by periodic measurements of blood glucose and A1C levels, with a goal of decreasing these levels toward the normal range. A1C monitoring is especially useful for evaluating long-term glycemic control.

Renal Function and Other Hematologic Parameters Monitoring
Inform patients that initial and periodic monitoring of hematologic parameters (e.g., hemoglobin/hematocrit and red blood cell indices) and renal function (e.g., serum creatinine) should be performed, at least on an annual basis [see Warnings and Precautions (5.3, 5.7)].

Distributed by:
Boehringer Ingelheim Pharmaceuticals, Inc.
Ridgefield, CT 06877 USA

Marketed by:
Boehringer Ingelheim Pharmaceuticals, Inc.
Ridgefield, CT 06877 USA
and
Eli Lilly and Company
Indianapolis, IN 46285 USA

Licensed from:
Boehringer Ingelheim International GmbH, Ingelheim, Germany

Copyright © 2014 Boehringer Ingelheim International GmbH
ALL RIGHTS RESERVED

Distributed by:

Physicians Total Care, Inc.

Tulsa, OK 74146

IT5571JG312014
300661-05

IT5645G
302118-04

MEDICATION GUIDE

JENTADUETO (JEN ta doo e' toe)
(linagliptin and metformin hydrochloride)
Tablets

Read this Medication Guide carefully before you start taking JENTADUETO and each time you get a refill. There may be new information. This information does not take the place of talking to your doctor about your medical condition or your treatment. If you have any questions about JENTADUETO, ask your doctor or pharmacist.

What is the most important information I should know about JENTADUETO?

Serious side effects can happen in people taking JENTADUETO, including:

1. Lactic Acidosis. Metformin, one of the medicines in JENTADUETO, can cause a rare but serious condition called lactic acidosis (a build-up of lactic acid in the blood) that can cause death. Lactic acidosis is a medical emergency and must be treated in the hospital.
  Stop taking JENTADUETO and call your doctor right away if you get any of the following symptoms of lactic acidosis:
  - feel very weak or tired
  - have unusual (not normal) muscle pain
  - have trouble breathing
  - have unusual sleepiness or sleep longer than usual
  - have sudden stomach or intestinal problems with nausea and vomiting or diarrhea
  - feel cold, especially in your arms and legs
  - feel dizzy or lightheaded
  - have a slow or irregular heart beat
  You have a higher chance of getting lactic acidosis if you:
  - have kidney problems. People whose kidneys are not working properly should not take JENTADUETO.
  - have liver problems
  - have congestive heart failure that requires treatment with medicines
  - drink alcohol very often, or drink a lot of alcohol in short-term ("binge" drinking)
  - get dehydrated (lose a large amount of body fluids). This can happen if you are sick with a fever, vomiting, or diarrhea. Dehydration can also happen when you sweat a lot with activity or exercise and do not drink enough fluids.
  - have certain x-ray tests with dyes or contrast agents that are injected into your body
  - have surgery
  - have a heart attack, severe infection, or stroke
  - are 80 years of age or older and have not had your kidneys tested
2. Inflammation of the pancreas (pancreatitis) which may be severe and lead to death.
  Certain medical problems make you more likely to get pancreatitis.
  Before you start taking JENTADUETO:
  Tell your doctor if you have ever had:
  - inflammation of your pancreas (pancreatitis)
  - stones in your gallbladder (gallstones)
  - a history of alcoholism
  - high blood triglyceride levels

Stop taking JENTADUETO and call your doctor right away if you have pain in your stomach area (abdomen) that is severe and will not go away. The pain may be felt going from your abdomen through to your back. The pain may happen with or without vomiting. These may be symptoms of pancreatitis.

What is JENTADUETO?

- JENTADUETO is a prescription medicine that contains 2 diabetes medicines, linagliptin and metformin. JENTADUETO can be used along with diet and exercise to lower blood sugar in adults with type 2 diabetes when treatment with both linagliptin and metformin is appropriate.
- JENTADUETO is not for people with type 1 diabetes.
- JENTADUETO is not for people with diabetic ketoacidosis (increased ketones in the blood or urine).
- If you have had pancreatitis in the past, it is not known if you have a higher chance of getting pancreatitis while you take JENTADUETO.
- It is not known if JENTADUETO is safe and effective in children under 18 years of age.

Who should not take JENTADUETO?

Do not take JENTADUETO if you:

- have kidney problems
- have a condition called metabolic acidosis or diabetic ketoacidosis (increased ketones in the blood or urine).
- are allergic to linagliptin, metformin, or any of the ingredients in JENTADUETO. See the end of this Medication Guide for a complete list of ingredients in JENTADUETO.Symptoms of a serious allergic reaction to JENTADUETO may include:
  - skin rash, itching, flaking or peeling
  - raised red patches on your skin (hives)
  - swelling of your face, lips, tongue and throat that may cause difficulty in breathing or swallowing
  - difficulty with swallowing or breathing

If you have any of these symptoms, stop taking JENTADUETO and contact your doctor or go to the nearest hospital emergency room right away.

What should I tell my doctor before using JENTADUETO?

Before you take JENTADUETO, tell your doctor if you:

- have or have had inflammation of your pancreas (pancreatitis).
- have kidney problems
- have liver problems
- have heart problems, including congestive heart failure
- drink alcohol very often, or drink a lot of alcohol in short term "binge" drinking
- are 80 years of age or older, you should not take JENTADUETO unless your kidneys have been checked and they are normal
- are going to get an injection of dye or contrast agents for an x-ray procedure. JENTADUETO will need to be stopped for a short time. Talk to your doctor about when you should stop JENTADUETO and when you should start JENTADUETO again. See "What is the most important information I should know about JENTADUETO?"
- have type 1 diabetes. JENTADUETO should not be used to treat people with type 1 diabetes.
- have any other medical conditions
- are pregnant or plan to become pregnant. It is not known if JENTADUETO will harm your unborn baby. If you are pregnant, talk with your doctor about the best way to control your blood sugar while you are pregnant.
- are breastfeeding or plan to breastfeed. It is not known if JENTADUETO passes into your breast milk. Talk with your doctor about the best way to feed your baby if you take JENTADUETO.

Tell your doctor about all the medicines you take, including prescription and non-prescription medicines, vitamins, and herbal supplements. JENTADUETO may affect the way other medicines work, and other medicines may affect how JENTADUETO works.

Especially tell your doctor if you take:

- other medicines that can lower your blood sugar
- rifampin (Rifadin®, Rimactane®, Rifater®, Rifamate®)*, an antibiotic that is used to treat tuberculosis

Ask your doctor or pharmacist for a list of these medicines if you are not sure if your medicine is one that is listed above.
Know the medicines you take. Keep a list of them and show it to your doctor and pharmacist when you get a new medicine.

How should I take JENTADUETO?

- Take JENTADUETO exactly as your doctor tells you to take it.
- Take JENTADUETO 2 times each day with meals. Taking JENTADUETO with meals may lower your chance of having an upset stomach.
- If you miss a dose, take it with food as soon as you remember. If you do not remember until it is time for your next dose, skip the missed dose and go back to your regular schedule. Do not take 2 doses of JENTADUETO at the same time.
- If you take too much JENTADUETO, call your doctor or Poison Control Center at 1-800-222-1222 or go to the nearest hospital emergency room right away.
- Your doctor may tell you to take JENTADUETO along with other diabetes medicines. Low blood sugar can happen more often when JENTADUETO is taken with certain other diabetes medicines. See "What are the possible side effects of JENTADUETO?"
- You may need to stop taking JENTADUETO for a short time. Call your doctor for instructions if you:
  - are dehydrated (have lost too much body fluid). Dehydration can occur if you are sick with severe vomiting, diarrhea, or fever, or if you drink a lot less fluid than normal.
  - plan to have surgery
  - are going to get an injection of dye or contrast agent for an x-ray procedure. See "What is the most important information I should know about JENTADUETO?" and "Who should not take JENTADUETO?"
- When your body is under some types of stress, such as fever, trauma (such as a car accident), infection, or surgery, the amount of diabetes medicine that you need may change. Tell your doctor right away if you have any of these conditions and follow your doctor’s instructions.
- Check your blood sugar as your doctor tells you to.
- Stay on your prescribed diet and exercise program while taking JENTADUETO.
- Your doctor will check your diabetes with regular blood tests, including your blood sugar levels and your hemoglobin A1C.
- Your doctor will do blood tests to check how well your kidneys are working before and during your treatment with JENTADUETO.

What are the possible side effects of JENTADUETO tablets?

JENTADUETO may cause serious side effects, including:

- See "What is the most important information I should know about JENTADUETO?"
  - low blood sugar (hypoglycemia).If you take JENTADUETO with another medication that can cause low blood sugar, such as sulfonylurea or insulin, your risk of getting low blood sugar is higher. The dose of your sulfonylurea medicine or insulin may need to be lowered while you take JENTADUETO. Signs and symptoms of low blood sugar may include:
    - headache
    - irritability
    - drowsiness
    - hunger
    - weakness
    - fast heart beat
    - dizziness
    - sweating
    - confusion
    - feeling jittery
  - Allergic (hypersensitivity) reactions.Serious allergic reactions can happen after your first dose or up to 3 months after starting JENTADUETO. Symptoms may include:
    - swelling of your face, lips, throat, and other areas on your skin
    - difficulty with swallowing or breathing
    - raised, red areas on your skin (hives)
    - skin rash, itching, flaking, or peeling
    If you have these symptoms, stop taking JENTADUETO and call your doctor or go to the nearest hospital emergency room right away.

The most common side effects of JENTADUETO include:

- stuffy or runny nose and sore throat
- diarrhea

These are not all the possible side effects of JENTADUETO. For more information, ask your doctor or pharmacist.

Tell your doctor if you have any side effects that bother you or that do not go away.

Call your doctor for medical advice about side effects. You may report side effects to FDA at 1-800-FDA-1088.

How should I store JENTADUETO tablets?

- Store JENTADUETO between 68°F and 77°F (20°C and 25°C).
- Keep tablets dry.

Keep JENTADUETO and all medicines out of the reach of children.

General information about the safe and effective use of JENTADUETO

Medicines are sometimes prescribed for purposes other than those listed in Medication Guides. Do not use JENTADUETO for a condition for which it was not prescribed. Do not give JENTADUETO to other people, even if they have the same symptoms you have. It may harm them.

This Medication Guide summarizes the most important information about JENTADUETO. If you would like more information, talk with your doctor. You can ask your pharmacist or doctor for information about JENTADUETO that is written for health professionals.

For more information, go to www.jentadueto.com (or scan the code below to go to www.jentadueto.com) or call Boehringer Ingelheim Pharmaceuticals, Inc. at 1-800-542-6257, or (TTY) 1-800-459-9906.

What are the ingredients in JENTADUETO?

Active Ingredients: linagliptin and metformin hydrochloride

Inactive Ingredients: arginine, corn starch, copovidone, colloidal silicon dioxide, magnesium stearate, titanium dioxide, propylene glycol, hypromellose, talc.

2.5 mg/500 mg and 2.5 mg/850 mg tablets also contain yellow ferric oxide.

2.5 mg/850 mg and 2.5 mg/1000 mg tablets also contain red ferric oxide.

What is type 2 diabetes?

Type 2 diabetes is a condition in which your body does not make enough insulin, and/or the insulin that your body produces does not work as well as it should. Your body can also make too much sugar. When this happens, sugar (glucose) builds up in the blood. This can lead to serious medical problems.

The main goal of treating diabetes is to lower your blood sugar to a normal level. High blood sugar can be lowered by diet and exercise, and by certain medicines when necessary.

Talk to your doctor about how to prevent, recognize, and take care of low blood sugar (hypoglycemia), high blood sugar (hyperglycemia), and other problems you have because of your diabetes.

This Medication Guide has been approved by the U. S. Food and Drug Administration.

Distributed by:
Boehringer Ingelheim Pharmaceuticals, Inc.
Ridgefield, CT 06877 USA

Marketed by:
Boehringer Ingelheim Pharmaceuticals, Inc.
Ridgefield, CT 06877 USA
and
Eli Lilly and Company
Indianapolis, IN 46285 USA

Licensed from:
Boehringer Ingelheim International GmbH
Ingelheim, Germany

Revised: July 2014

Distributed by:

Physicians Total Care, Inc.

Tulsa, OK 74146

*The brands listed are trademarks of their respective owners and are not trademarks of Boehringer Ingelheim Pharmaceuticals, Inc. The makers of these brands are not affiliated with and do not endorse Boehringer Ingelheim Pharmaceuticals, Inc., or its products.

Copyright © 2014 Boehringer Ingelheim International GmbH
ALL RIGHTS RESERVED

IT5571JG312014
300661-05

IT5645G
302118-04

PACKAGE LABEL

Jentadueto (linagliptin and metformin hydrochloride) tablets
NDC: 54868-6461